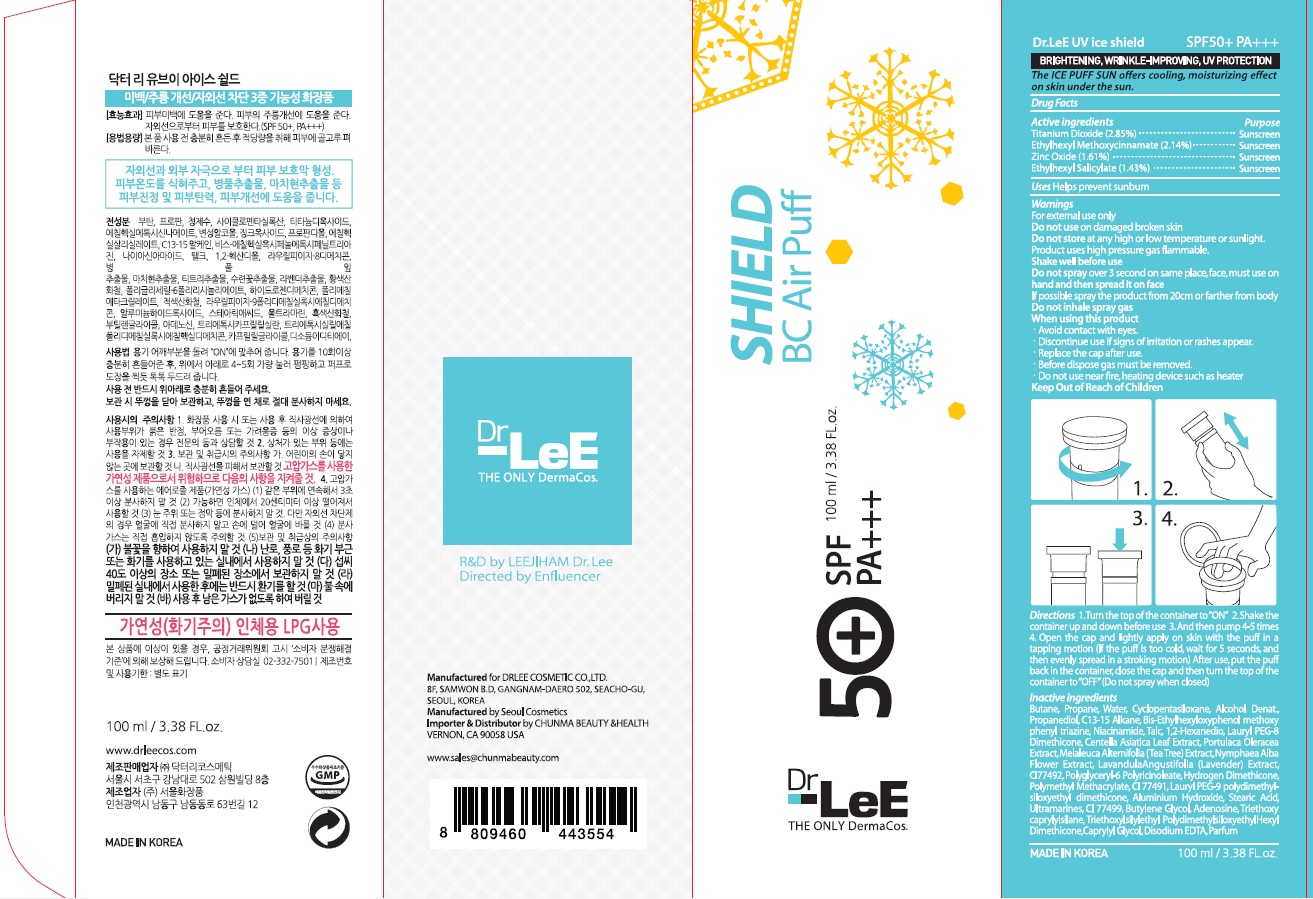 DRUG LABEL: Dr LeE UV ICE SHIELD
NDC: 71367-010 | Form: CREAM
Manufacturer: DRLEECOSMETIC
Category: otc | Type: HUMAN OTC DRUG LABEL
Date: 20170411

ACTIVE INGREDIENTS: Titanium Dioxide 2.85 g/100 mL; Octinoxate 2.14 g/100 mL; Zinc Oxide 1.61 g/100 mL; Octisalate 1.43 g/100 mL
INACTIVE INGREDIENTS: Butane; Water

ACTIVE INGREDIENT

Active ingredients: Titanium Dioxide 2.85%, Ethylhexyl Methoxycinnamate 2.14%, Zinc Oxide 1.61%, Ethylhexyl Salicylate 1.43%

INACTIVE INGREDIENT

Inactive ingredients: Butane, Propane, Water, Cyclopentasiloxane, Alcohol Denat., Propanediol, C13-15 Alkane, Bis-Ethylhexyloxyphenol methoxyphenyl triazine, Niacinamide, Talc, 1,2-Hexanedio, Lauryl PEG-8 Dimethicone, Centella Asiatica Leaf Extract, Portulaca Oleracea Extract, Melaleuca Alternifolia (Tea Tree) Extract, Nymphaea Alba Flower Extract, LavandulaAngustifolia (Lavender) Extract, CI 77492, Polyglyceryl-6 Polyricinoleate, Hydrogen Dimethicone, Polymethyl Methacrylate, CI 77491, Lauryl PEG-9 polydimethylsiloxyethyl dimethicone, Aluminium Hydroxide, Stearic Acid, Ultramarines, CI 77499, Butylene Glycol, Adenosine, Triethoxycaprylylsilane, Triethoxylsilylethyl PolydimethylsiloxyethylHexyl Dimethicone, Caprylyl Glycol, Disodium EDTA, Parfum

PURPOSE

Purpose: Sunscreen

WARNINGS

For external use only Do not use on damaged broken skin Do not store at any high or low temperature or sunlight. Product uses high pressure gas flammable. Shake well before use Do not spray over 3 second on same place, face, must use on hand and then spread it on face If possible spray the product from 20cm or farther from body Do not inhale spray gas When using this product

Avoid contact with eyes. Discontinue use if signs of irritation or rashes appear. Replace the cap after use. Before dispose gas must be removed. Do not use near fire, heating device such as heater

Keep Out of Reach of Children

DESCRIPTION

Uses: Helps prevent sunburn

Directions 1. Turn the top of the container to “ON” 2. Shake the container up and down before use 3. And then pump 4-5 times 4. Open the cap and lightly apply on skin with the puff in a tapping motion (If the puff is too cold, wait for 5 seconds, and then evenly spread in a stroking motion) 5. After use, put the puff back in the container, close the cap and then turn the top of the container to “OFF” (Do not spray when closed)